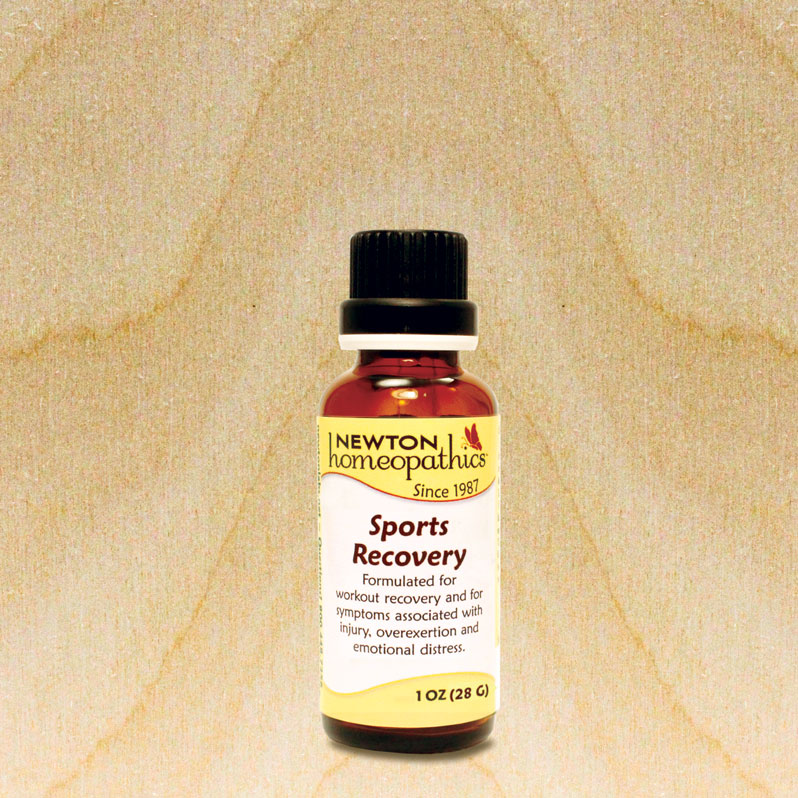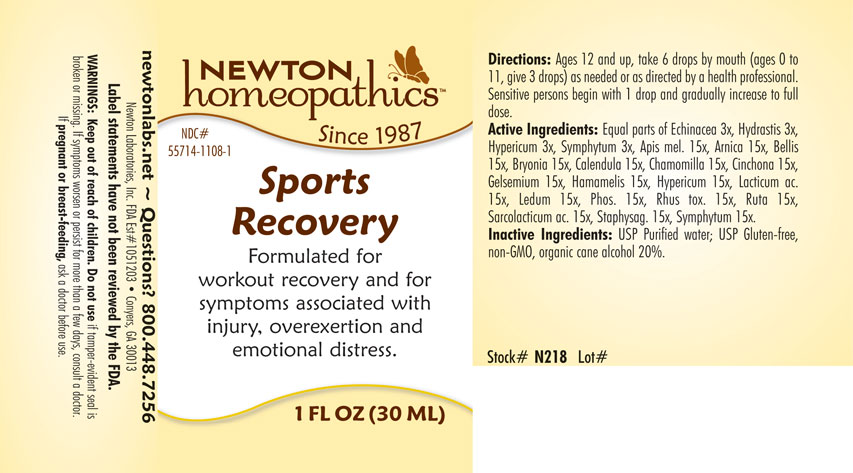 DRUG LABEL: Sports Recovery
NDC: 55714-1108 | Form: LIQUID
Manufacturer: Newton Laboratories, Inc.
Category: homeopathic | Type: HUMAN OTC DRUG LABEL
Date: 20160725

ACTIVE INGREDIENTS: APIS MELLIFERA 15 [hp_X]/1 mL; ARNICA MONTANA 15 [hp_X]/1 mL; BELLIS PERENNIS 15 [hp_X]/1 mL; BRYONIA ALBA ROOT 15 [hp_X]/1 mL; CALENDULA OFFICINALIS FLOWERING TOP 15 [hp_X]/1 mL; MATRICARIA RECUTITA 15 [hp_X]/1 mL; CINCHONA OFFICINALIS BARK 15 [hp_X]/1 mL; GELSEMIUM SEMPERVIRENS ROOT 15 [hp_X]/1 mL; HAMAMELIS VIRGINIANA ROOT BARK/STEM BARK 15 [hp_X]/1 mL; HYPERICUM PERFORATUM 15 [hp_X]/1 mL; LACTIC ACID, DL- 15 [hp_X]/1 mL; LEDUM PALUSTRE TWIG 15 [hp_X]/1 mL; PHOSPHORUS 15 [hp_X]/1 mL; TOXICODENDRON PUBESCENS LEAF 15 [hp_X]/1 mL; RUTA GRAVEOLENS FLOWERING TOP 15 [hp_X]/1 mL; LACTIC ACID, L- 15 [hp_X]/1 mL; DELPHINIUM STAPHISAGRIA SEED 15 [hp_X]/1 mL; COMFREY ROOT 15 [hp_X]/1 mL; ECHINACEA, UNSPECIFIED 3 [hp_X]/1 mL; GOLDENSEAL 3 [hp_X]/1 mL
INACTIVE INGREDIENTS: ALCOHOL

Sports Recovery

OTC - KEEP OUT OF REACH OF CHILDREN SECTION

Warnings: Keep out of reach of children.

OTC - PREGNANCY OR BREAST FEEDING SECTION

If pregnant or breast-feeding, ask a doctor before use.

WARNINGS SECTION

Warning:Keep out of reach of children. Do not use if tamper - evident seal is broken or missing. If symptoms worsen or persist for more than a few days, consult a doctor. If pregnant or breast-feeding, ask a doctor before use.

QUESTIONS SECTION

www.newtonlabs.net Newton Laboratories, Inc. FDA Est # 1051203 - Conyers, GA 30012
Questions? 1.800.448.7256

INACTIVE INGREDIENT SECTION

Inactive Ingredients: USP Purified Water; USP Gluten-free, non-GMO, organic cane dispensing alcohol 20%.

OTC - PURPOSE SECTION

Formulated for work out recovery and for symptoms associated with injury, overexertion and emotional distress.

DOSAGE & ADMINISTRATION SECTION

Directions: ORAL USE ONLY - SHAKE WELL. Ages 12 and up, take 6 drops by mouth (ages 0 to 11, give 3 drops) as needed or as directed by a healthcare professional. Sensitive persons begin with 1 drop and gradually increase to full dose.

INDICATIONS & USAGE SECTION

Sports Recovery Formulated for workout recovery and for symptoms associated with injury, overexertion and emotional distress.

OTC - ACTIVE INGREDIENT SECTION

Apis mel. 15x, Arnica 15x, Bellis 15x, Bryonia 15x, Calendula 15x, Chamomilla 15x, Cinchona 15x, Gelsemium 15x, Hamamelis 15x, Hypericum 15x, Lacticum acidum 15x, Ledum 15x, Phosphorus 15x, Rhus toxicodendron 15x, Ruta 15x, Sarcolacticum ac. 15x, Staphysag. 15x, Symphytum 15x, Echinacea 3x, Hydrastis 3x, Hypericum 3x, Symphytum 3x.